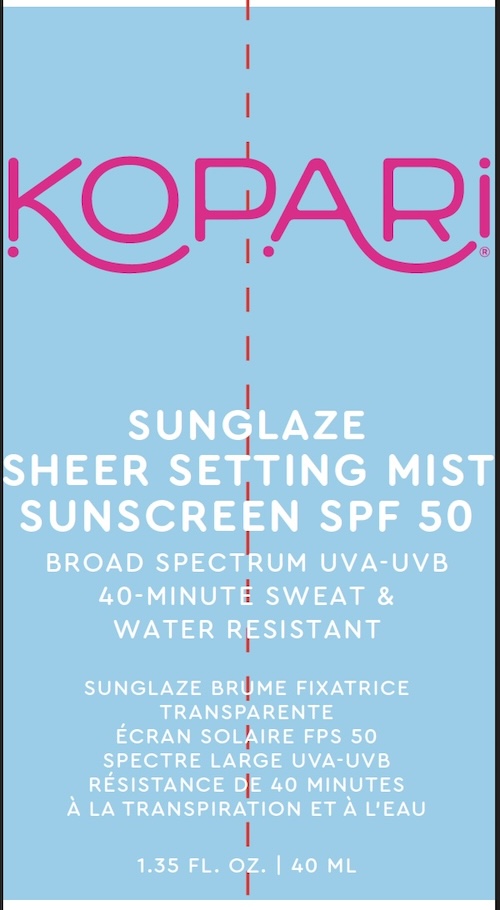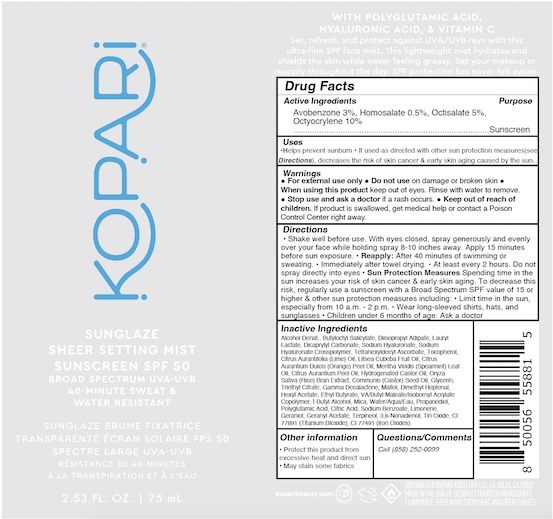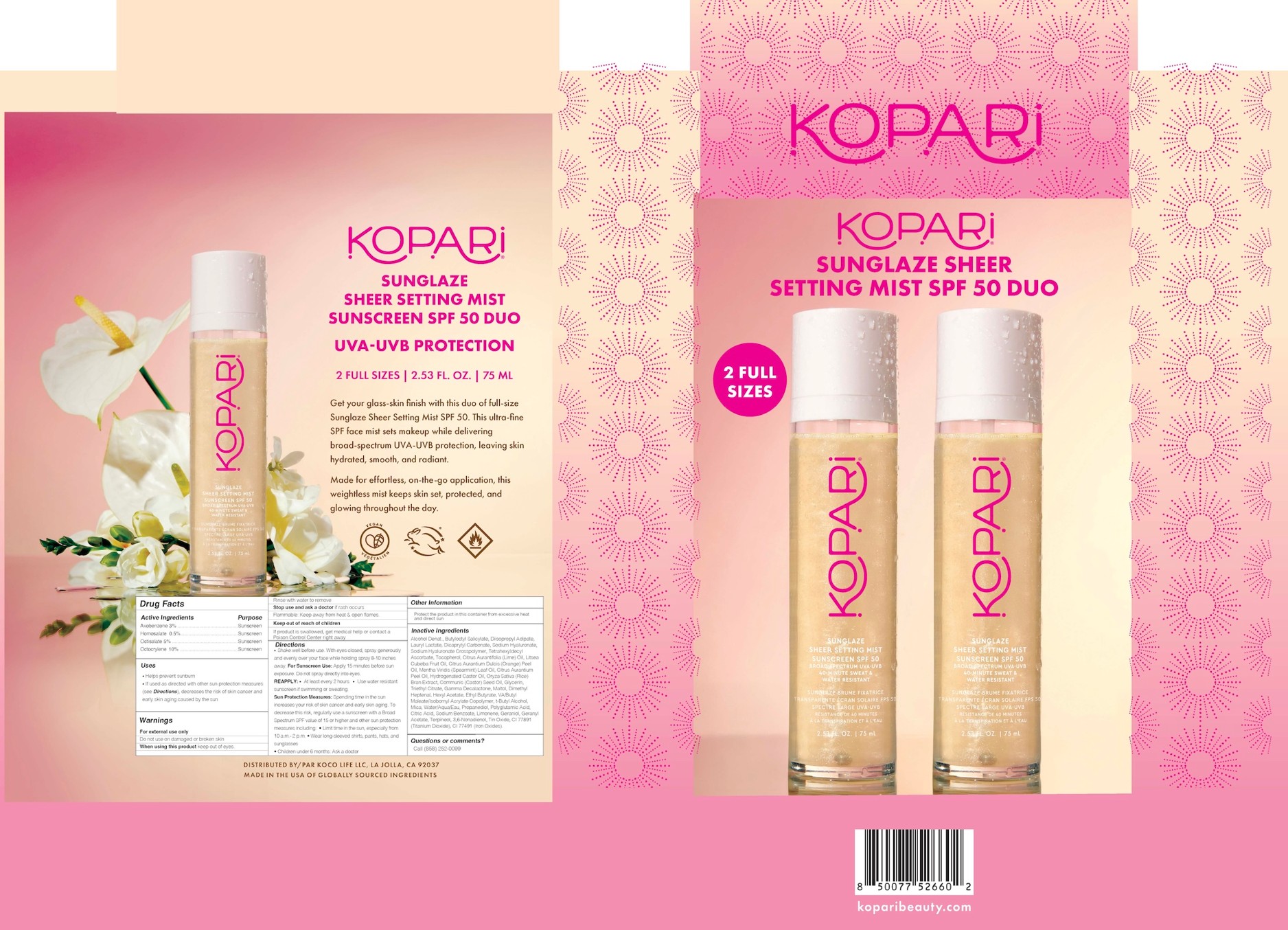 DRUG LABEL: Sunglaze Sheer Setting Mist Sunscreen SPF50
NDC: 84130-011 | Form: SPRAY
Manufacturer: Koco Life LLC
Category: otc | Type: HUMAN OTC DRUG LABEL
Date: 20260205

ACTIVE INGREDIENTS: HOMOSALATE 5 mg/1 mL; OCTISALATE 50 mg/1 mL; OCTOCRYLENE 100 mg/1 mL; AVOBENZONE 30 mg/1 mL
INACTIVE INGREDIENTS: BUTYLOCTYL SALICYLATE; LAURYL LACTATE; HYALURONATE SODIUM; PEG-9 DIGLYCIDYL ETHER/SODIUM HYALURONATE CROSSPOLYMER; MALTOL; LIME OIL, COLD PRESSED; ETHYL BUTYRATE; BITTER ORANGE OIL; TRIETHYL CITRATE; DIISOPROPYL ADIPATE; HYDROGENATED CASTOR OIL; GERANIOL; TOCOPHEROL; RICE BRAN; CASTOR OIL; GLYCERIN; DIBUTYL MALEATE; TERT-BUTYL ALCOHOL; MICA; SODIUM BENZOATE; GERANYL ACETATE; ORANGE OIL, COLD PRESSED; WATER; TITANIUM DIOXIDE; TERPINEOL; LIMONENE, (+)-; ALCOHOL; 2,6-DIMETHYL-5-HEPTENAL; LITSEA OIL; .GAMMA.-DECALACTONE; HEXYL ACETATE; PROPANEDIOL; POLYGLUTAMIC ACID (1200 MW); CITRIC ACID MONOHYDRATE; STANNOUS OXIDE; DICAPRYLYL CARBONATE; TETRAHEXYLDECYL ASCORBATE; SPEARMINT OIL; FERRIC OXIDE RED

Sunglaze Sheer Setting Mist Sunscreen SPF50

Active ingredients

Avobenzone 3%, Homosalate 0.5%, Octisalate 5%, Octyocrylene 10%

Purpose

Avobenzone 3%, Homosalate 0.5%, Octisalate 5%, Octyocrylene 10%.................Sunscreen

Uses

•Helps prevent sunburn

• If used as directed with other sun protection measures(see Directions), decreases the risk of skin cancer & early skin aging caused by the sun.

Warnings

For external use only

● Do not use on damage or broken skin

● When using this product keep out of eyes. Rinse with water to remove.

● Stop use and ask a doctor if a rash occurs.

● Keep out of reach of children. If product is swallowed, get medical help or contact a Poison Control Center right away.

Directions

Shake well before use. With eyes closed, spray generously and evenlyover your face while holding spray 8-10 inches away. Apply 15 minutesbefore sun exposure. • Reapply: After 40 minutes of swimming orsweating. • Immediately after towel drying. • At least every 2 hours. Do notspray directly into eyes • Sun Protection Measures Spending time in thesun increases your risk of skin cancer & early skin aging. To decrease thisrisk, regularly use a sunscreen with a Broad Spectrum SPF value of 15 orhigher & other sun protection measures including: • Limit time in the sun,especially from 10 a.m. - 2 p.m. • Wear long-sleeved shirts, hats, andsunglasses • Children under 6 months of age: Ask a doctor

Inactive Ingredients

Alcohol Denat., Butyloctyl Salicylate, Diisopropyl Adipate, Lauryl Lactate, Dicaprylyl Carbonate, Sodium Hyaluronate, Sodium Hyaluronate Crosspolymer, Tetrahexyldecyl Ascorbate, Tocopherol, Citrus Aurantifolia (Lime) Oil, Litsea Cubeba Fruit Oil, Citrus Aurantium Dulcis (Orange) Peel Oil, Mentha Viridis (Spearmint) Leaf Oil, Citrus Aurantium Peel Oil, Hydrogenated Castor Oil, Oryza Sativa (Rice) Bran Extract, Communis (Castor) Seed Oil, Glycerin, Triethyl Citrate, Gamma Decalactone, Maltol, Dimethyl Heptenal, Hexyl Acetate, Ethyl Butyrate, VA/Butyl Maleate/Isobornyl Acrylate Copolymer, t-Butyl Alcohol, Mica, Water/Aqua/Eau, Propanediol, Polyglutamic Acid, Citric Acid, Sodium Benzoate, Limonene, Geraniol, Geranyl Acetate, Terpineol, 3,6-Nonadienol, Tin Oxide, CI 77891 (Titanium DIoxide), CI 77491 (Iron Oxides).

Other Information

• Protect this product fromexcessive heat and direct sun

• May stain some fabrics

Questions/Comments

Call (858) 252-0099

PACKAGE LABEL

Kopari

Sunglaze

Sheer Setting Mist

Sunscreen SPF 50

Broad Spectrum UVA-UVB

40-Minute Sweat &

Water Resistant

2.53 Fl. Oz. | 75 mL